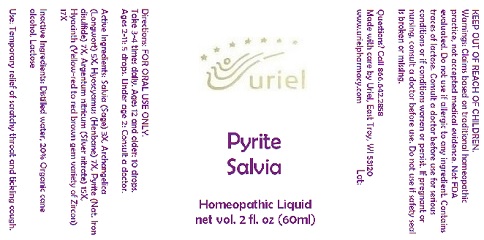 DRUG LABEL: Pyrite Salvia
NDC: 48951-8104 | Form: LIQUID
Manufacturer: Uriel Pharmacy Inc.
Category: homeopathic | Type: HUMAN OTC DRUG LABEL
Date: 20180430

ACTIVE INGREDIENTS: SAGE 3 [hp_X]/1 mL; ANGELICA ARCHANGELICA ROOT 5 [hp_X]/1 mL; HYOSCYAMUS NIGER LEAF 7 [hp_X]/1 mL; FERROUS DISULFIDE 7 [hp_X]/1 mL; SILVER 15 [hp_X]/1 mL; HYACINTHUS ORIENTALIS WHOLE 17 [hp_X]/1 mL
INACTIVE INGREDIENTS: WATER; ALCOHOL; LACTOSE

Pyrite Salvia

INDICATIONS AND USAGE

Directions: FOR ORAL USE ONLY.

DOSAGE AND ADMINISTRATION

Take 3-4 times daily. Ages 12 and older: 10 drops. Ages 2-11: 5 drops. Under age 2: Consult a doctor.

ACTIVE INGREDIENT

Active Ingredients: Salvia (Sage) 3X, Archangelica (Longwort) 5X, Hyoscyamus (Henbane) 7X, Pyrite (Nat. Iron disulfide) 7X, Argentum nitricum (Silver nitrate) 15X, Hyacinth (Yellow-red to red brown gem variety of Zircon) 17X

INACTIVE INGREDIENT

Inactive Ingredients: Distilled water, 20% Organic cane alcohol, Lactose

PURPOSE

Use: Temporary relief of scratchy throat and tickling cough.

KEEP OUT OF REACH OF CHILDREN.

WARNINGS

Warnings: Claims based on traditional homeopathic practice, not accepted medical evidence. Not FDA evaluated. Do not use if allergic to any ingredient. Contains traces of lactose. Consult a doctor before use for serious conditions or if conditions worsen or persist. If pregnant or nursing, consult a doctor before use. Do not use if safety seal is broken or missing.

QUESTIONS

Questions? Call 866.642.2858 Made with care by Uriel, East Troy, WI 53120 www.urielpharmacy.com